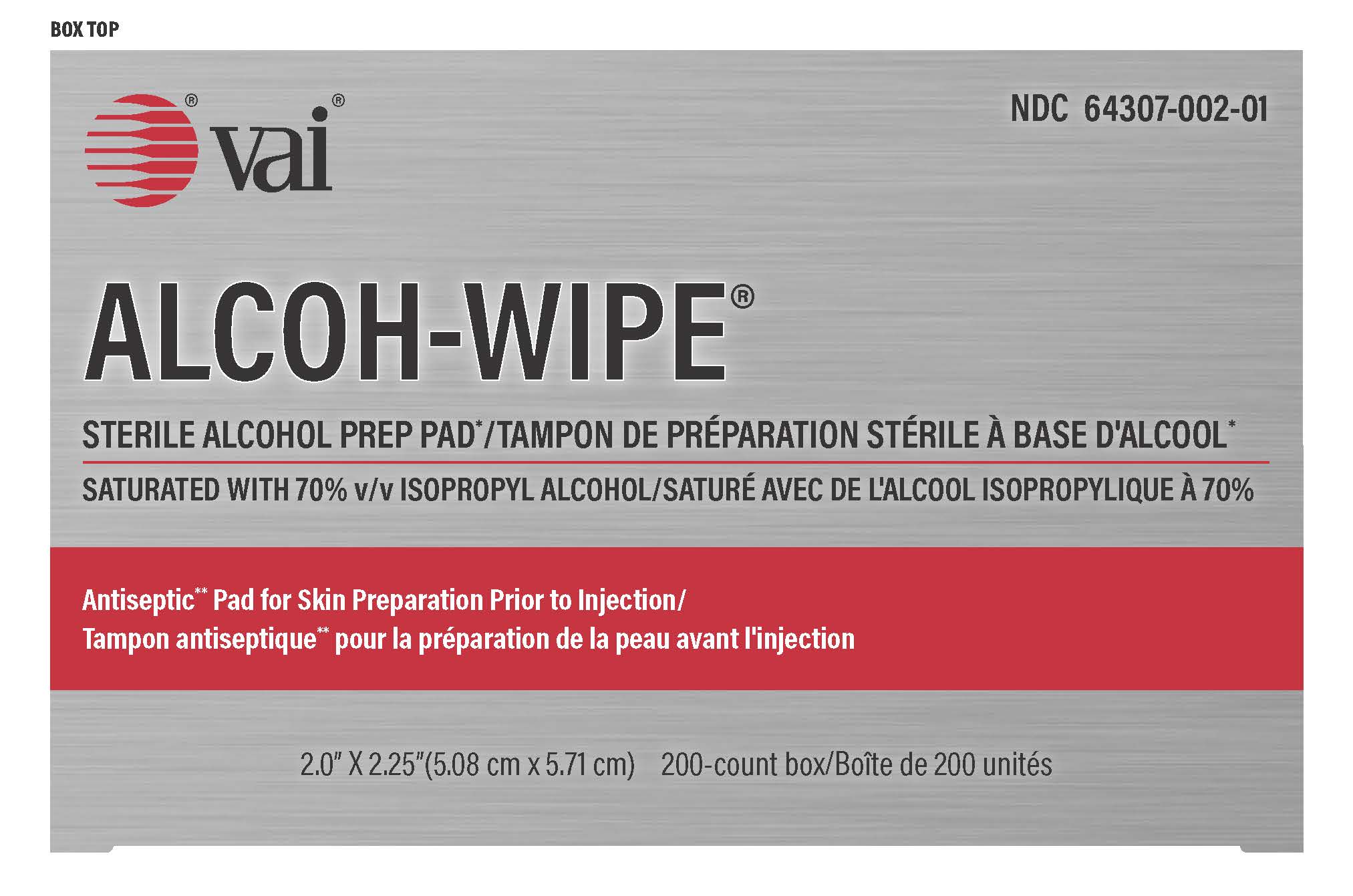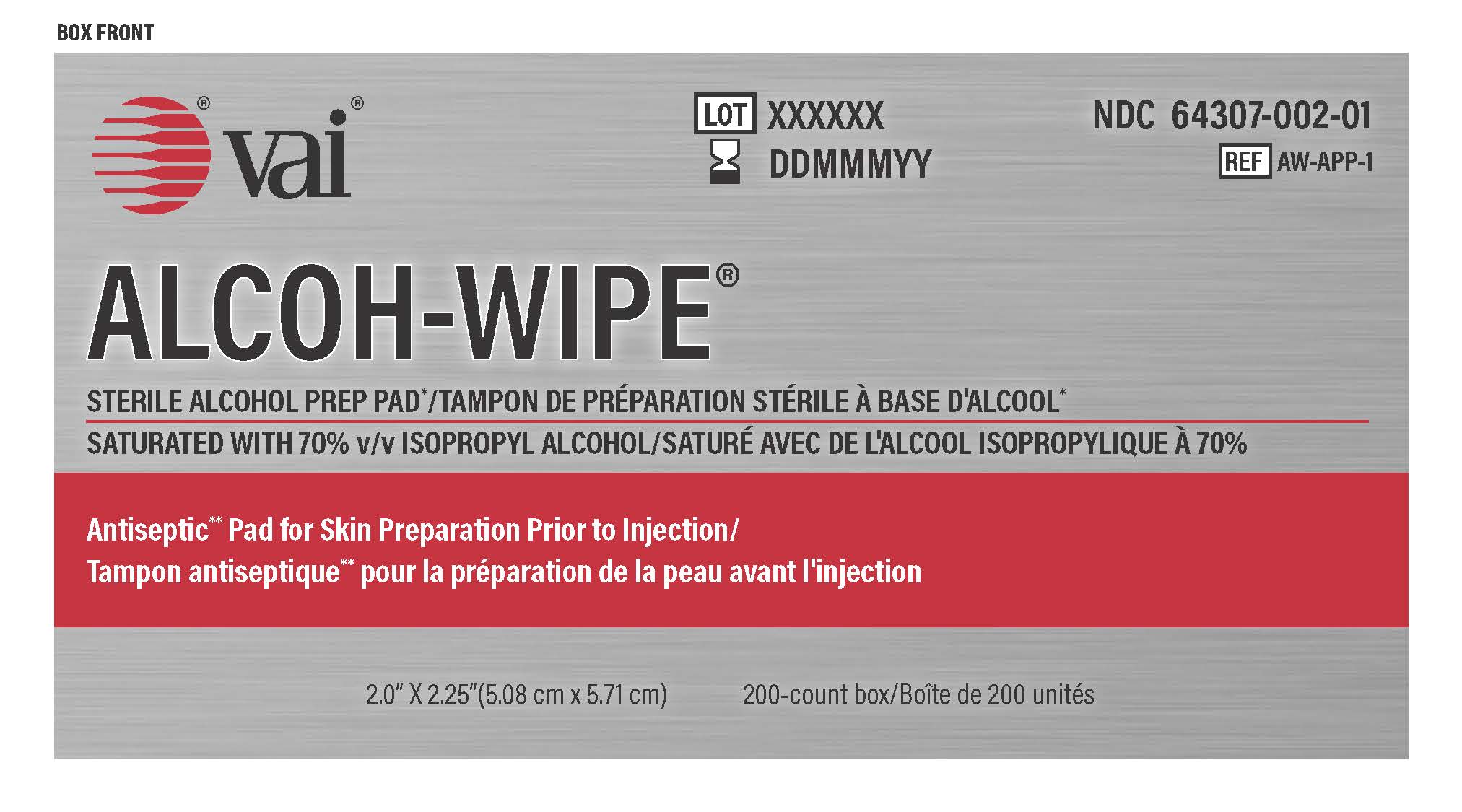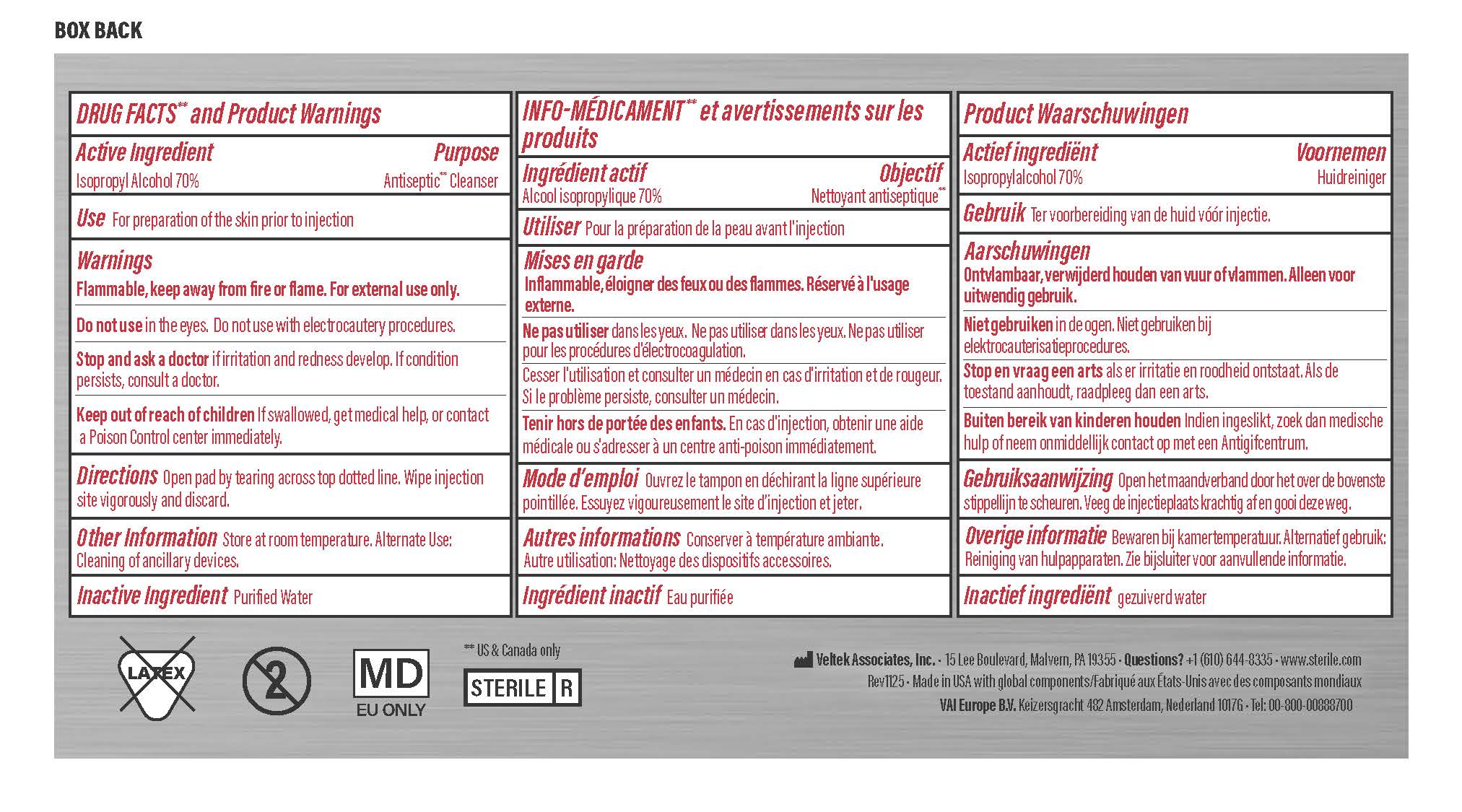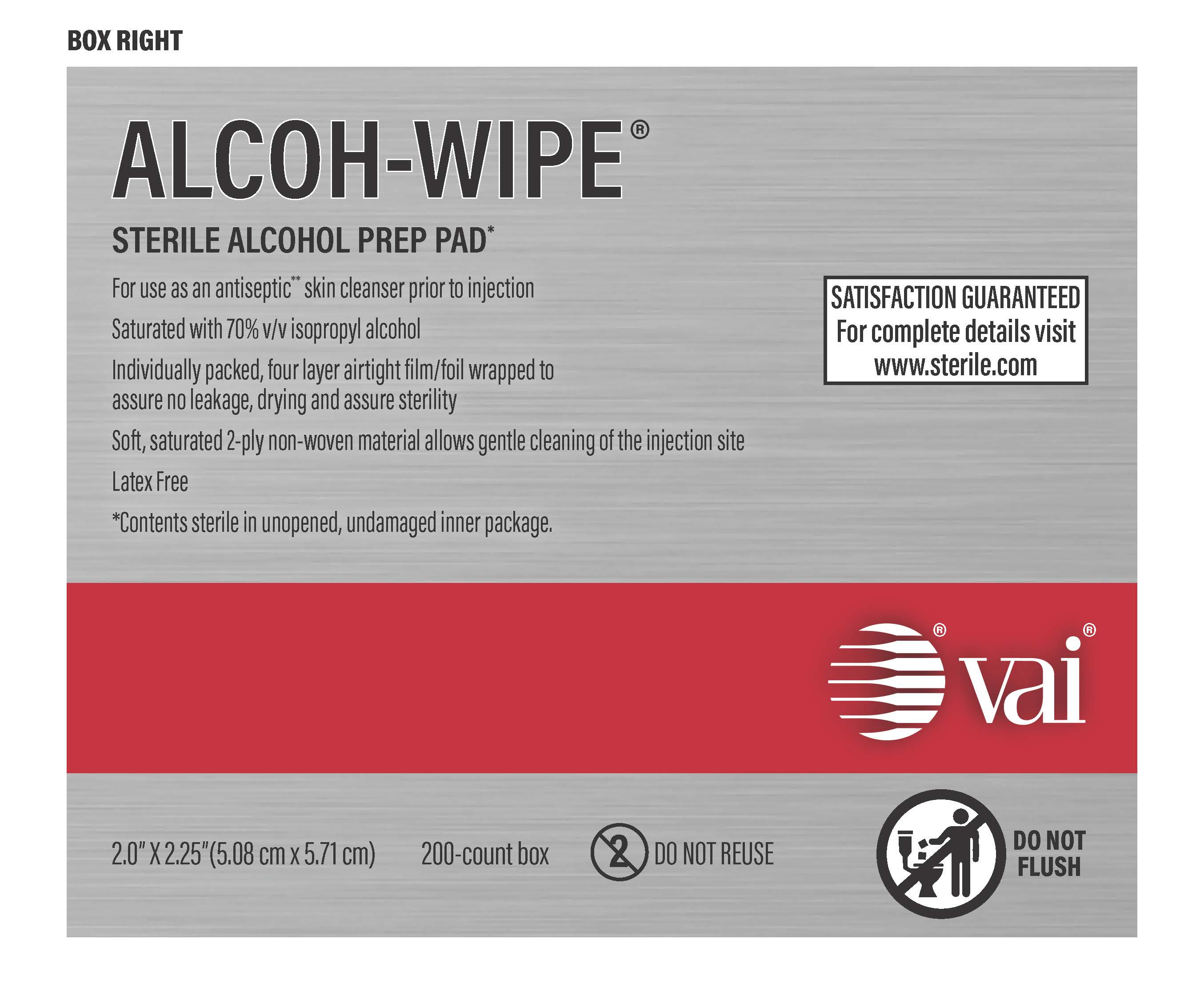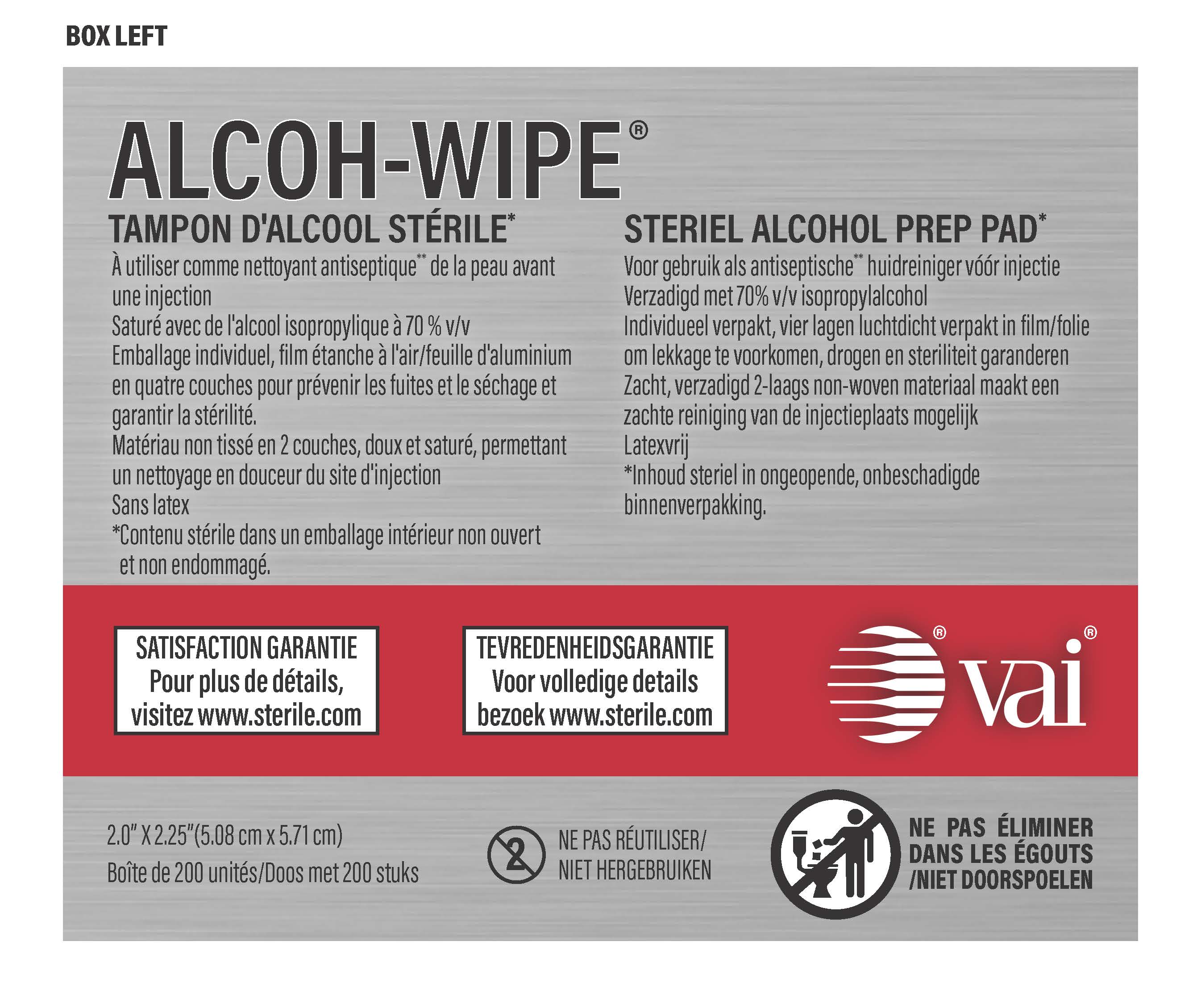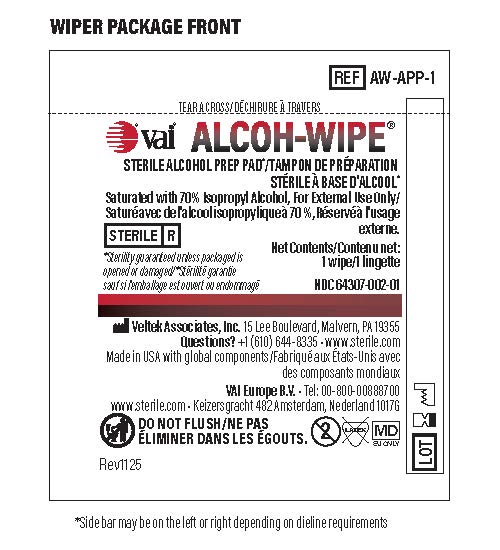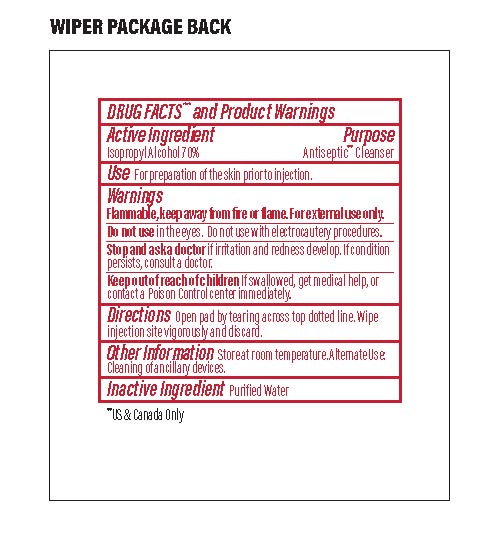 DRUG LABEL: ALCOH-WIPE
NDC: 64307-002 | Form: SWAB
Manufacturer: Veltek Associates, Inc.
Category: otc | Type: HUMAN OTC DRUG LABEL
Date: 20251210

ACTIVE INGREDIENTS: ISOPROPYL ALCOHOL 0.7 mL/1 mL
INACTIVE INGREDIENTS: WATER 0.3 mL/1 mL

ALCOH-WIPE

ACTIVE INGREDIENT

Isopropyl Alcohol 70%

PURPOSE

Antiseptic Cleanser

INDICATIONS AND USAGE

Use For preparation of the skin prior to injection

WARNINGS

Flammable, keep away from fire or flame. For external use only.

Do not use in the eyes. Do not use with electrocautery procedures.

ASK DOCTOR

Stop and ask a doctor if irritation and redness develop. If condition persists, consult a doctor.

Keep out of reach of children. If swallowed, get medical help, or contact a Poison Control center immediately.

DOSAGE AND ADMINISTRATION

Directions Open pad by tearing across top dotted line.

Wipe injection site vigorously and discard.

Other Information Store at room temperature. Alternate Use: Cleaning of ancillary devices.

INACTIVE INGREDIENT

Purified Water

Questions? +1 (610) 644-8335 www.sterile.com